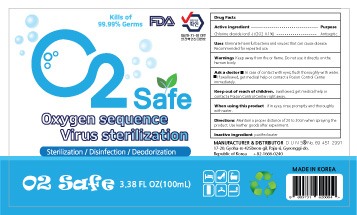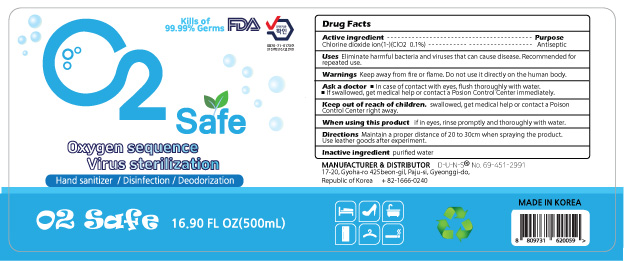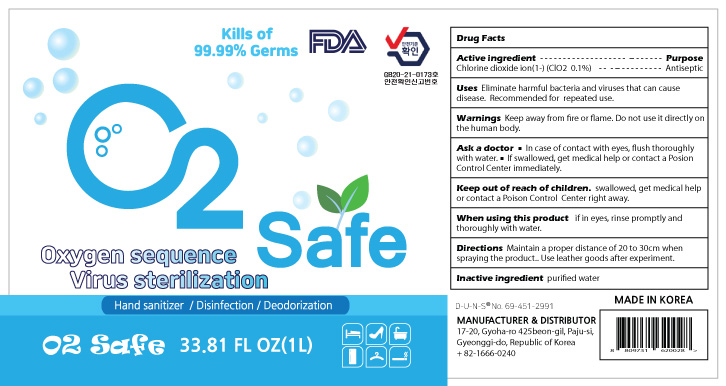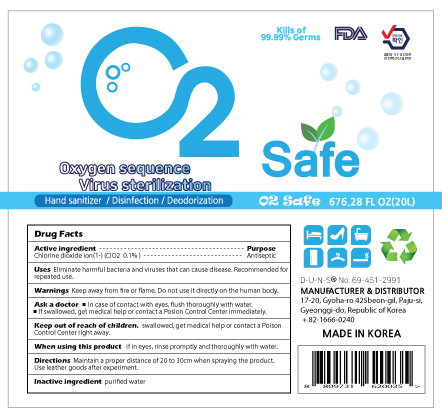 DRUG LABEL: O2safe
NDC: 80928-201 | Form: LIQUID
Manufacturer: O2NS
Category: otc | Type: HUMAN OTC DRUG LABEL
Date: 20230101

ACTIVE INGREDIENTS: CHLORITE ION 0.1 g/100 mL
INACTIVE INGREDIENTS: WATER

80928-201

Active ingredient

Chlorine dioxide ion(1-) (CLO2 0.1%)

Purpose

Antiseptic

Uses

Eliminate harmful bacteria and viruses that can cause disease. Recommended for repeated use.

Warnings

Keep away from fire or flame. Do not use it directly on the human body.

Ask a doctor

In case of contact with eyes, flush thoroughly with water.

If swallowed, get medical help or contact a Posion Control Center immediately.

Keep out of reach of children.

swallowed, get medical help or contact a Poison Control Center right away.

When using this product

if in eyes, rinse promptly and thoroughly with water.

Directions

Maintain a proper distance of 20 to 30cm when spraying the product. Use leather goods after experiment.

Inactive ingredient

purified water